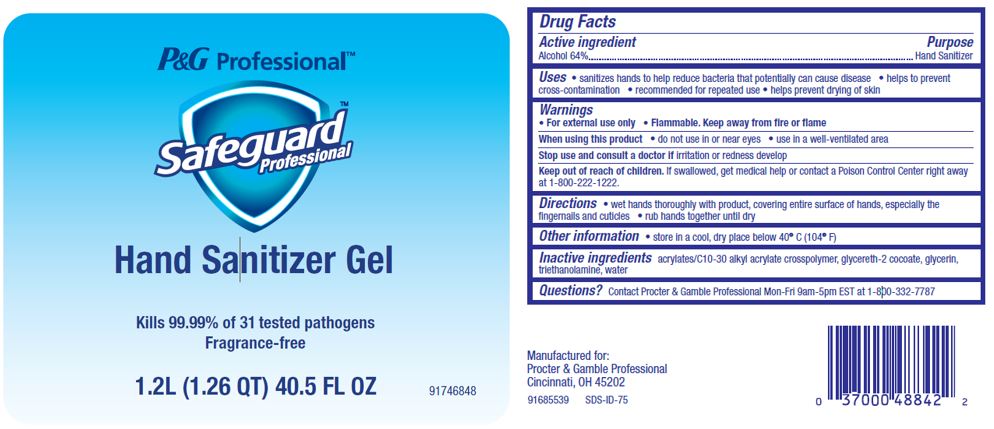 DRUG LABEL: Safeguard
NDC: 37000-603 | Form: GEL
Manufacturer: The Procter & Gamble Manufacturing Company
Category: otc | Type: HUMAN OTC DRUG LABEL
Date: 20251218

ACTIVE INGREDIENTS: ALCOHOL 64 g/100 mL
INACTIVE INGREDIENTS: TROLAMINE; GLYCERIN; GLYCERETH-2 COCOATE; CARBOMER INTERPOLYMER TYPE A (ALLYL SUCROSE CROSSLINKED)

Safeguard®
Hand Sanitizer Gel

Drug Facts

Active Ingredient

Ethanol 64%

Purpose

Hand Sanitizer

Uses

- For handwashing to decrease bacteria on the skin
- Recommended for repeated use

Warnings

- For external use only
- Flammable, keep away from fire or flame

When using this product

- Do not use in or near eyes
- Use in a well-ventilated area

- Discontinue use if irritation and redness develop

Keep out of reach of children

In case of accidental ingestion, seek medical attention or contact a poison control center immediately.

Directions

- Receive a small amount of liquid into palm of hand
- Rub thoroughly over all surfaces of both hands
- Rub hands together until dry

Other information

- Store in a cool dry place below 104° F

Inactive ingredients

Acrylates/C10-30 Alkyl Acrylate Crosspolymer, glycereth-2-cocoate, glycerine, triethanolamine, water

Questions?

Contact Procter & Gamble Professional® Mon-Fri 9am - 5pm EST at 1-800-332-7787

PRINCIPAL DISPLAY PANEL - 1.2L Bag Label

Procter & Gamble
Professional®

Safeguard®

Hand Sanitizer Gel
Alcohol Hand Sanitizer Gel

1.2L (1.26 QT) 40.5 FL OZ